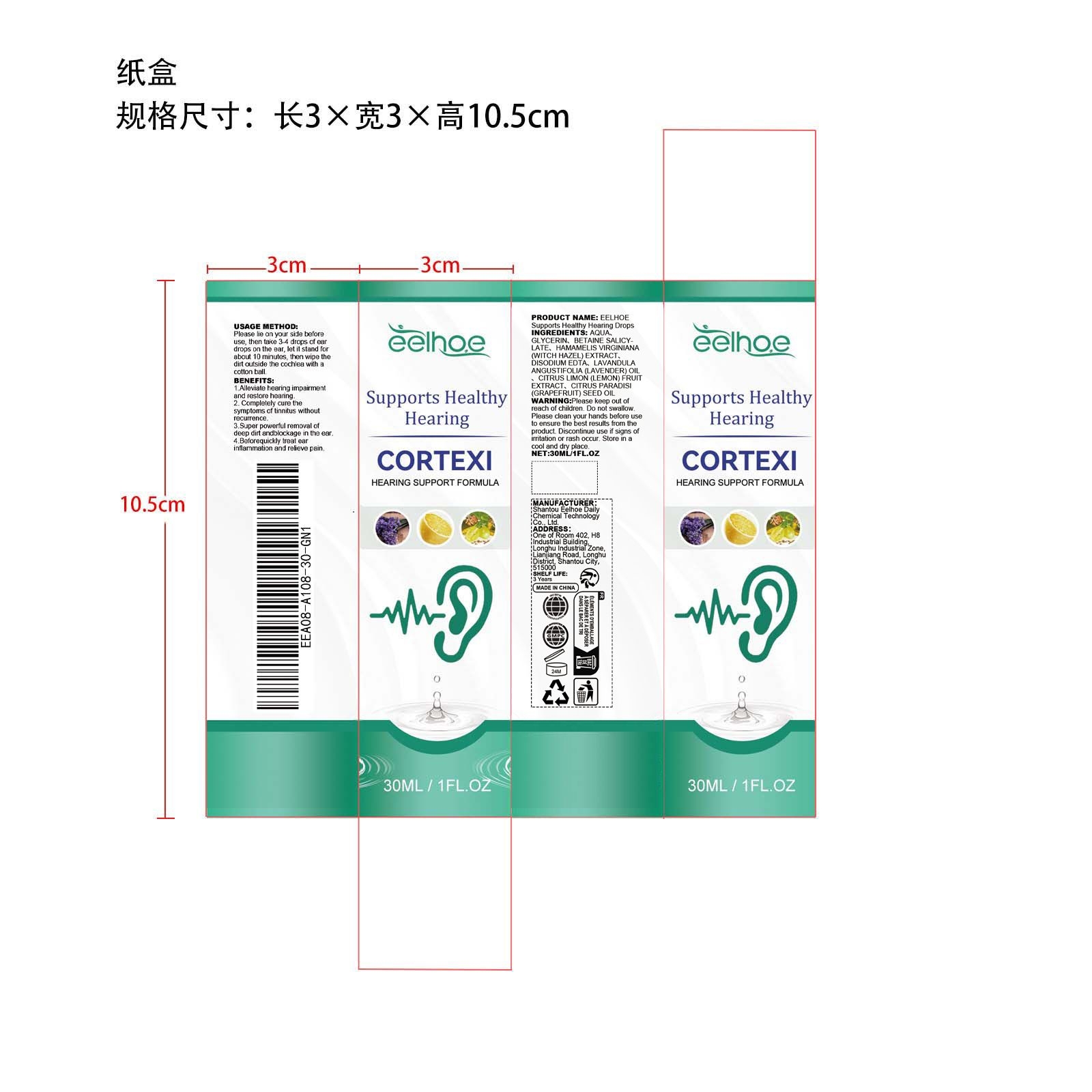 DRUG LABEL: EELHOE Supports Healthy Hearing Drops
NDC: 85064-026 | Form: LIQUID
Manufacturer: Shantou Eelhoe Daily Chemical Technology Co., Ltd.
Category: otc | Type: HUMAN OTC DRUG LABEL
Date: 20251215

ACTIVE INGREDIENTS: HAMAMELIS VIRGINIANA (WITCH HAZEL) LEAF WATER 0.15 mg/30 mg; CITRUS LIMON (LEMON) FRUIT OIL 0.006 mg/30 mg; CITRUS PARADISI (GRAPEFRUIT) SEED OIL 0.006 mg/30 mg; LAVANDULA ANGUSTIFOLIA (LAVENDER) OIL 0.006 mg/30 mg
INACTIVE INGREDIENTS: GLYCERIN 1.5 mg/30 mg; BETAINE SALICYLATE 0.6 mg/30 mg; AQUA 27.702 mg/30 mg; DISODIUM EDTA-COPPER 0.03 mg/30 mg

ACTIVE INGREDIENT

HAMAMELIS VIRGINIANA (WITCH HAZEL) EXTRACT、LAVANDULA ANGUSTIFOLIA (LAVENDER) OIL、CITRUS LIMON (LEMON) FRUIT EXTRACT、CITRUS PARADISI (GRAPEFRUIT) SEED OIL

PURPOSE

1. Alleviate hearing impairment and restore hearing.

2. Completely cure the symptoms of tinnitus without recurrence.

3. Super powerful removal of deep dirt and blockage in the ear.

4. Before quickly treat ear inflammation and relieve pain.

WHEN USING

Please lie on your side before use, then take 3-4 drops of ear drops on the ear, let it stand for about 10 minutes, then wipe the dirt outside the cochlea with a cotton bail

WARNINGS

Please keep out of reach of children. Do not swallow.Please clean your hands before use to ensure the best results from the product. Discontinue use if signs of irritation or rash occur. Store in a cool and dry place.

DO NOT USE

Discontinue use if signs of irritation or rash occur.

STOP USE

Discontinue use if signs of irritation or rash occur.

KEEP OUT OF REACH OF CHILDREN

Please keep out of reach of children. Do not swallow.

STORAGE AND HANDLING

Store in a cool and dry place.

INACTIVE INGREDIENT

AQUA、GLYCERIN、BETAINE SALICYLATE、DISODIUM EDTA

INDICATIONS AND USAGE

Please lie on your side before use, then take 3-4 drops of ear drops on the ear, let it stand for about 10 minutes, then wipe the dirt outside the cochlea with a cotton bail

DOSAGE AND ADMINISTRATION

Please lie on your side before use, then take 3-4 drops of ear drops on the ear, let it stand for about 10 minutes, then wipe the dirt outside the cochlea with a cotton bail